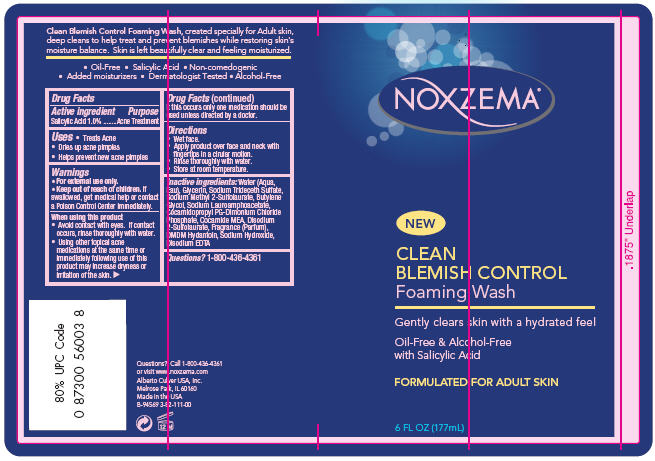 DRUG LABEL: Noxzema
NDC: 12488-1300 | Form: SOAP
Manufacturer: Alberto-Culver USA Inc. 
Category: otc | Type: HUMAN OTC DRUG LABEL
Date: 20091217

ACTIVE INGREDIENTS: Salicylic Acid 0.01 mL/1 mL
INACTIVE INGREDIENTS: Water; Edetate Disodium; Glycerin; Butylene Glycol; Sodium Hydroxide

Drug Facts

Active ingredient

Salicylic Acid 1.0%

Purpose

Acne Treatment

Uses

- Treats Acne
- Dries up acne pimples
- Helps prevent new acne pimples

Warnings

- For external use only.
- Keep out of reach of children. If swallowed, get medical help or contact a Poison Control Center immediately.

When using this product

- Avoid contact with eyes. If contact occurs, rinse thoroughly with water.
- Using other topical acne medications at the same time or immediately following use of this product may increase dryness or irritation of the skin.
  If this occurs only one medication should be used unless directed by a doctor.

Directions

- Wet face.
- Apply product over face and neck with fingertips in a cirular motion.
- Rinse thoroughly with water.
- Store at room temperature.

Inactive ingredients

Water (Aqua, Eau), Glycerin, Sodium Trideceth Sulfate, Sodium Methyl 2-Sulfolaurate, Butylene Glycol, Sodium Lauroamphoacetate, Cocamidopropyl PG-Dimonium Chloride Phosphate, Cocamide MEA, Disodium 2-Sulfolaurate, Fragrance (Parfum), DMDM Hydantoin, Sodium Hydroxide, Disodium EDTA

Questions?

1-800-436-4361

PRINCIPAL DISPLAY PANEL - 177 mL Bottle

NOXZEMA®

NEW

CLEAN
BLEMISH CONTROL
Foaming Wash

Gently clears skin with a hydrated feel

Oil-Free & Alcohol-Free
with Salicylic Acid

FORMULATED FOR ADULT SKIN

6 FL OZ (177mL)